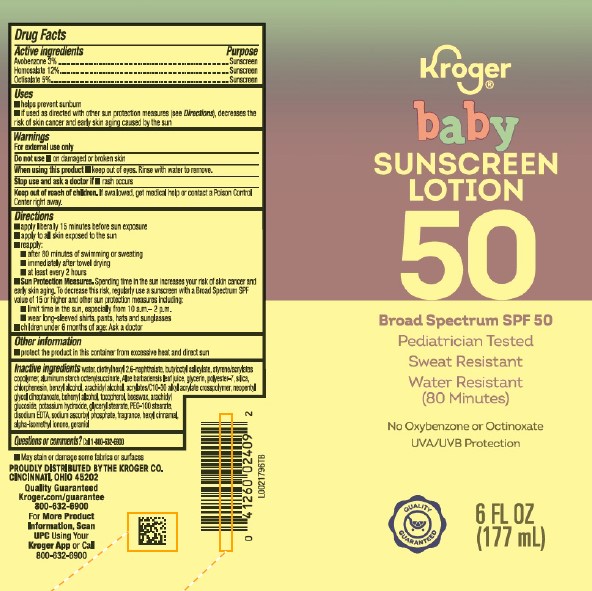 DRUG LABEL: Avobenzone, Homosalate, Octisalate
NDC: 59450-947 | Form: LOTION
Manufacturer: The Kroger Co.
Category: otc | Type: HUMAN OTC DRUG LABEL
Date: 20260227

ACTIVE INGREDIENTS: AVOBENZONE 30 mg/1 mL; HOMOSALATE 120 mg/1 mL; OCTISALATE 50 mg/1 mL
INACTIVE INGREDIENTS: WATER; DIETHYLHEXYL 2,6-NAPHTHALATE; BUTYLOCTYL SALICYLATE; STYRENE/ACRYLAMIDE COPOLYMER (500000 MW); ALUMINUM STARCH OCTENYLSUCCINATE; ALOE VERA LEAF; GLYCERIN; POLYESTER-7; SILICON DIOXIDE; CHLORPHENESIN; BENZYL ALCOHOL; ARACHIDYL ALCOHOL; CARBOMER COPOLYMER TYPE B (ALLYL PENTAERYTHRITOL CROSSLINKED); NEOPENTYL GLYCOL DIHEPTANOATE; DOCOSANOL; TOCOPHEROL; YELLOW WAX; ARACHIDYL GLUCOSIDE; POTASSIUM HYDROXIDE; GLYCERYL MONOSTEARATE; PEG-100 STEARATE; EDETATE DISODIUM ANHYDROUS; SODIUM ASCORBYL PHOSPHATE; .ALPHA.-HEXYLCINNAMALDEHYDE; ISOMETHYL-.ALPHA.-IONONE; GERANIOL

Kroger D47.001/D47AA
Sunscreen Lotion for Babies SPF 50

Active ingredients

Avobenzone 3%

Homosalate 12%

Octisalate 5%

Purpose

Sunscreen

Uses

- helps prevent sunburn
- if used as directed with other sun protection measures (See Directions), decreases the risk of skin cancer and early skin aging caused by the sun

Warnings

For external use only

Do not use

- on damaged or broken skin

When using this product

- keep out of eyes. Rinse with water to remove.

Stop use and ask a doctor if

- rash occurs

Keep out of reach of children.

If swallowed, get medical help or contact a Poison Control right away.

Directions

- apply liberaly 15 minutes before sun exposure
- apply to all skin exposed to the sun
- reapply:
- after 80 minutes of swimming or sweating
- immediately after towel drying
- at least every 2 hours
- Sun Protection Measures. Spending time in the sun increases your risk of skin cancer and early skin aging. To decrease this risk, regularly use a sunscreen with Broad Spectrum SPF value of 15 or higher and other sun protection measures including:
- limit time in the sun, especialy from 10 a.m. -2 p.m.
- wear long-sleeved shirts, pants, hats and sunglasses
- children under 6 months of age: Ask a doctor

Other information

- protect the product in this container from excessive heat and direct sun

inactive ingredients

water, diethylhexyl 2,6-naphthalate, butyloctyl salicylate, styrene/acrylates copolymer, aluminum starch octenylsuccinate, Aloe barbadensis leaf juice, glycerin, polyester-7, silica, chlorphenesin, benzyl alcohol, arachidyl alcohol, acrylates/C10-30 alkyl acrylate crosspolymer, neopentyl glycol diheptanoate, behenyl alcohol, tocopherol, beeswax, arachidyl glucoside, potassium hydroxide, glyceryl stearate, PEG-100 stearate, disodium EDTA, sodium ascorbyl phosphate, fragrance, hexyl cinnamal, alpha-isomethyl ionone, geraniol

Questions or comments?

Call 1-800-632-6900

Disclaimer

- May stain or damage some fabrics or surfaces

Adverse Reaction

PROUDLY DISTRIBUTED BY THE KROGER CO.

CINCINNATI, OHIO 45202

Quality Guaranteed Kroger.com/guarantee 800-632-6900

For More Product Information, Scan UPC Using Your Kroger App or Call 800-632-6900

Principal Panel Display

Kroger®

baby

SUNSCREEN LOTION 50

Broad Spectrum SPF 50

Pediatrician Tested

Sweat Resistant

Water Resistant (80 Minutes)

No Oxybenxone or Octinoxate

UVA/UVB Protection

QUALITY GUARANTEED

6 FL OZ (177 mL)